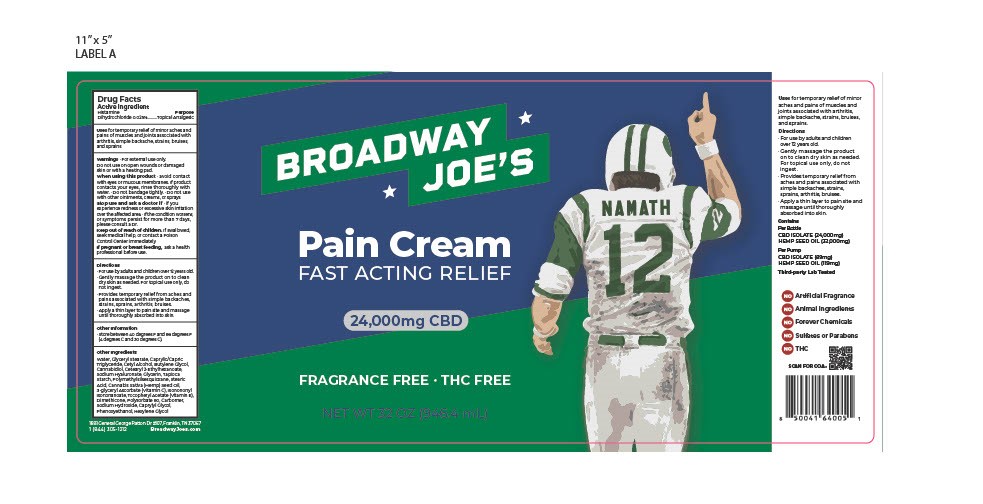 DRUG LABEL: histamine dihydrochloride
NDC: 83088-8120 | Form: CREAM
Manufacturer: USA Hemp Store LLC
Category: otc | Type: HUMAN OTC DRUG LABEL
Date: 20241217

ACTIVE INGREDIENTS: HISTAMINE DIHYDROCHLORIDE 0.00025 g/1 mL
INACTIVE INGREDIENTS: ISONONYL ISONONANOATE; GLYCERYL STEARATE SE; CETYL ALCOHOL; STEARIC ACID; DIMETHICONE 350; POLYSORBATE 80; CANNABIDIOL; HEXYLENE GLYCOL; HYALURONIC ACID; 3-GLYCERYL ASCORBATE; VITAMIN A PALMITATE; ALUMINUM STARCH OCTENYLSUCCINATE; ETHYL ACRYLATE/METHACRYLIC ACID/STEARETH-20 METHACRYLATE COPOLYMER; GLYCERIN; BUTYLENE GLYCOL DICAPRATE; CAPRYLYL GLYCOL; WATER; SODIUM HYDROXIDE; TOCOPHERYL RETINOATE; CETEARYL OLIVATE; CANNABIS SATIVA SEED OIL; PHENOXYETHANOL; CAPRYLIC/CAPRIC ACID

Broadway Joe's Pain Cream 32oz

Broadway Joe's Pain Cream

Histamine dihydrochloride

Braodway Joe's Pain Cream

Water, Glyceryl Stearate, Caprylic/Capric, Triglyceride, Cetyl Alcohol, Butylene Glycol, Cannabidiol, Cetearyl 2- thylhexanoate, Sodium Hyaluronate, Glycerin, Tapioca Starch, Polymethylsilsesquioxane, Stearic Acid, Cannabis Sativa (Hemp) Seed Oil, 3-glyceryl Ascorbate (Vitamin C), Isonononyl Isononanoate, Tocopheryl Acetate (Vitamin E), Dimethicone, Polysorbate 80, Carbomer, Sodium Hydroxide, Caprylyl Glycol, Phenoxyethanol, Hexylene Glycol

Broadway Joe's Pain Cream

- For use by adults and children over 13 yrs old.
- Gently massage the product on to clean dry skin as needed.
- For topical use only, do not ingest.
- Provides temporary relief from aches and pains associated with simple backaches,strains, sprains, arthritis, bruises.
- Apply a thin layer to pain site and massage until thoroughly absorbed into skin.

Broadway Joe's Pain Cream

Topical Analgesic

Broadway Joe's Pain Cream

Store between 40 degrees F and 86 degrees F (4 degrees C and 30 degrees C).

Broadway Joe's Pain Cream

Warnings · For external use only.
Do not use on open wounds or damaged skin or with a heating pad.

When using this product · avoid contact with eyes or mucous membranes. If product contacts your eyes, rinse thoroughly with water. Do not bandage tightly. · Do not use with other ointments, creams, or sprays.

Stop use and ask a doctor if you experience redness or excessive skin irritation over the affected area. · If the condition worsens, or symptoms persist for more than 7 days please consult a Dr.

Keep out of reach of children. If swallowed, seek medical help, or contact a Poison Control Center immediately.

If pregnant or breast feeding, ask a health professional before use.

Broadway Joe's Pain Cream

Stop use and ask a doctor if you experience redness or excessive skin irritation over the affected area. · If the condition worsens,
or symptoms persist for more than 7 days, please consult a Dr.

Broadway Joe's Pain Cream

Topical Analgesic

Broadway Joe's Pain Cream

Keep out of reach of children. If swallowed, seek medical help or contact a poison control center immediately.